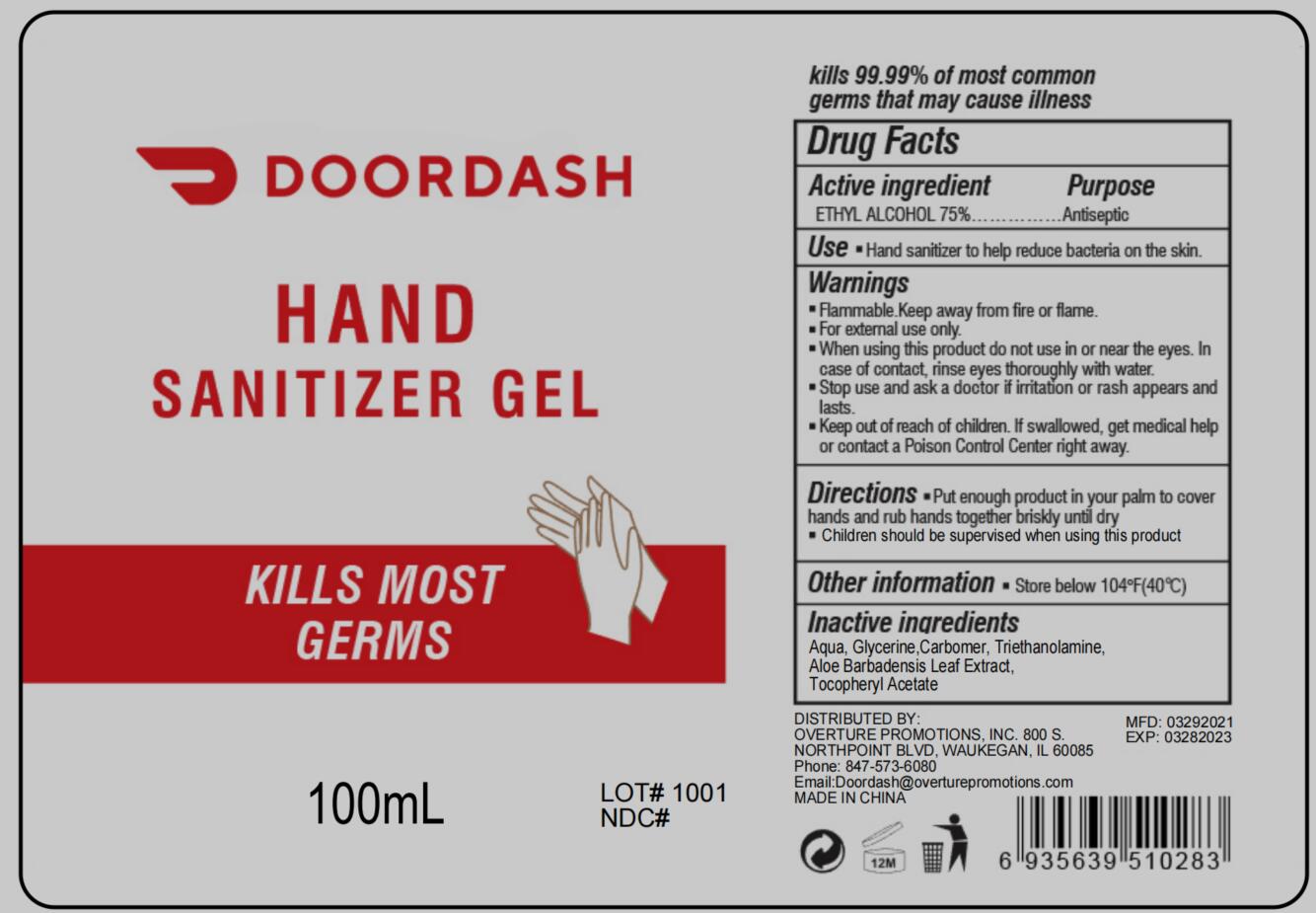 DRUG LABEL: hand sanitizer
NDC: 73788-110 | Form: GEL
Manufacturer: Hangzhou Huiji Biotechnology Co., Ltd.
Category: otc | Type: HUMAN OTC DRUG LABEL
Date: 20220224

ACTIVE INGREDIENTS: ALCOHOL 75 mL/100 mL
INACTIVE INGREDIENTS: WATER; GLYCERIN; ALOE VERA LEAF; TROLAMINE; CARBOMER 934; .ALPHA.-TOCOPHEROL ACETATE

73788-110 hand sanitizer 75% Ethyl Alcohol

Active Ingredient

Ethyl Alcohol 75%

Purpose

Antiseptic

Use

Hand sanitizer to help reduce bacteria on the skin

WARNINGS

Flammable. Keep away from fire or flame. For external use only.
- When using this product do not use in or near the eyes. ln case of contact, rinse eyes thoroughly with water.
Stop use and ask a doctor if irritation or rash appears and lasts.

- Keep out of reach of children. lf swallowed, get medical help or contact a Poison Control Center right away.

Directions

Put enough product in your palm to cover hands and rub hands together briskly until dry
Children should be supervised when using this product

Inactive ingredients

Water, Glycerin,Carbomer , Triethanolamine, Aloe Barbadensisleaf extract,Tocopheryl acetate